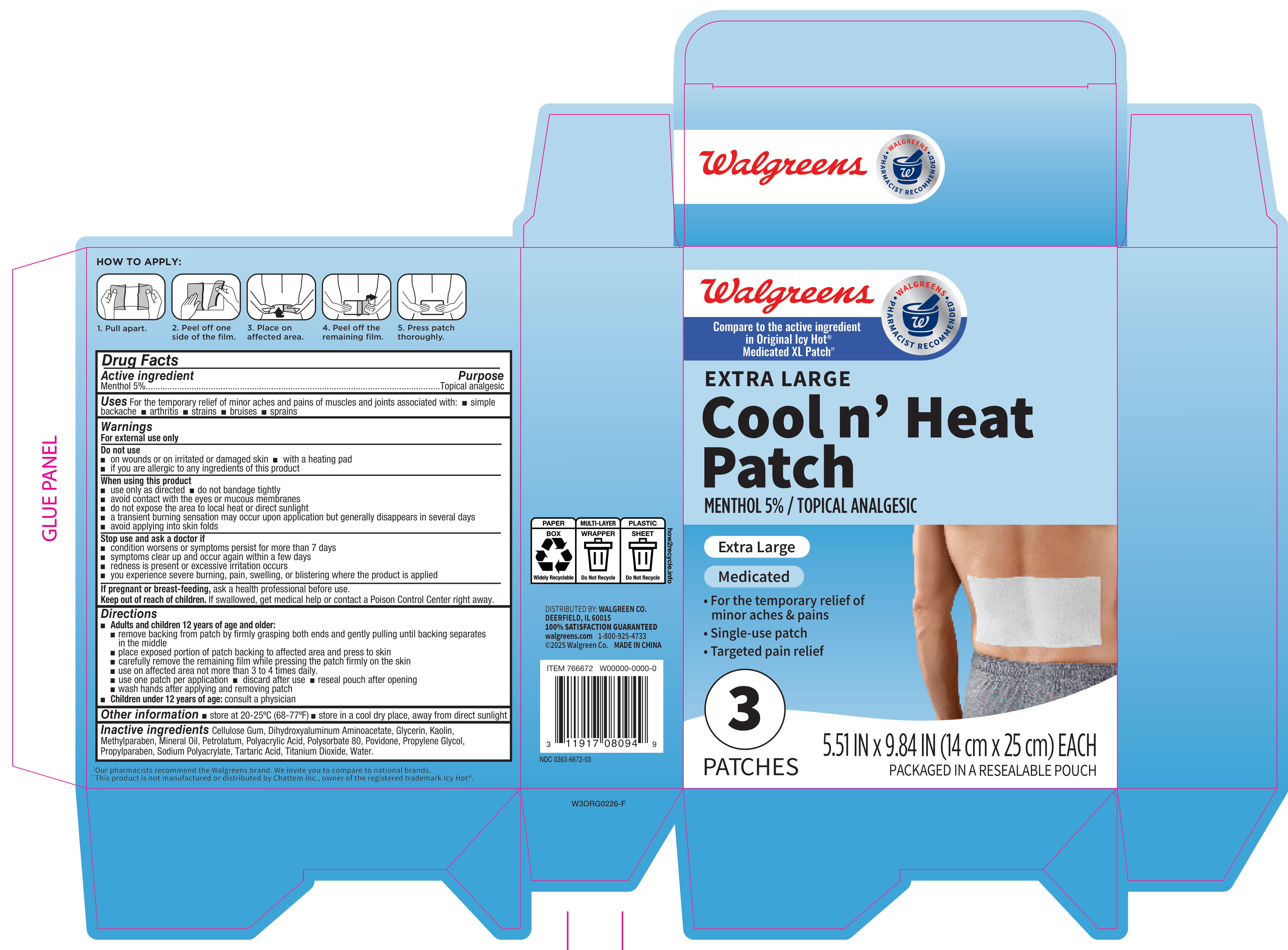 DRUG LABEL: Walgreens Cool N Heat Patch XL
NDC: 0363-6672 | Form: PATCH
Manufacturer: Walgreen Co.
Category: otc | Type: HUMAN OTC DRUG LABEL
Date: 20260210

ACTIVE INGREDIENTS: MENTHOL, UNSPECIFIED FORM 50 mg/1 g
INACTIVE INGREDIENTS: SODIUM POLYACRYLATE (8000 MW); POVIDONE; POLYSORBATE 80; METHYLPARABEN; DIHYDROXYALUMINUM AMINOACETATE; PROPYLPARABEN; TARTARIC ACID; KAOLIN; WATER; TITANIUM DIOXIDE; CELLULOSE GUM; GLYCERIN; PROPYLENE GLYCOL; MINERAL OIL; PETROLATUM; POLYACRYLIC ACID (8000 MW)

Walgreens Cool N Heat Patch XL 766672

Active ingredient

Menthol 5%

Purpose

Topical analgesic

Uses

For the temporary relief of minor aches and pains of muscles and joints associated with:

- simple backache
- arthritis
- strains
- bruises
- sprains

Warnings

For external use only

Do not use

- on wounds or on irritated or damaged skin
- with a heating pad
- if you are allergic to any ingredients of this product

When using this product

- use only as directed
- do not bandage tightly
- avoid contact with the eyes or mucous membranes
- do not expose the area to local heat or direct sunlight
- a transient burning sensation may occur upon application but generally disappears in several days
- avoid applying into skin folds

Stop use and ask a doctor if

- condition worsens or symptoms persist for more than 7 days
- symptoms clear up and occur again within a few days
- redness is present or excessive irritation occurs
- you experience severe burning, pain, swelling, or blistering where the product is applied

If pregnant or breast-feeding,

ask a health professional before use.

Keep out of reach of children.

If swallowed, get medical help or contact a Poison Control Center right away.

Directions

- Adults and children 12 years of age and older:
- remove backing from patch by firmly grasping both ends and gently pulling until backing separates in the middle
- place exposed portion of patch backing to affected area and press to skin
- carefully remove the remaining film while pressing the patch firmly on the skin
- use on affected area not more then 3 to 4 times daily.
- use one patch per application
- discard after use
- reseal pouch after opening
- wash hands after applying and removing patch
- Chilren under 12 years of age: consult a physician

Other information

- store at 20-25°C (68-77°F)
- store in a cool dry place, away from direct sunlight

Inactive ingredients

Cellulose Gum, Dihydroxyaluminum Aminoacetate, Glycerin, Kaolin, Methylparaben, Mineral Oil, Petrolatum, Polyacrylic Acid, Polysorbate 80, Povidone, Propylene Glycol, Propylparaben, Sodium Polyacrylate, Tartaric Acid, Titanium Dioxide, Water.

Principal Display Panel - 5.51 IN x 9.84 IN Carton Label

Walgreens

Compare to the active ingredient in Original Icy Hot® Medicated XL Patch††

Extra Large

Cool n' Heat

Patch

Menthol 5% / Topical Analgesic

Extra Large

Medicated

- For the temporary relief of minor aches & pains
- Single-use patch
- Targeted pain relief

3 PATCHES

5.51 IN x 9.84 IN (14 cm x 25 cm) EACH

Packaged in a resealable pouch